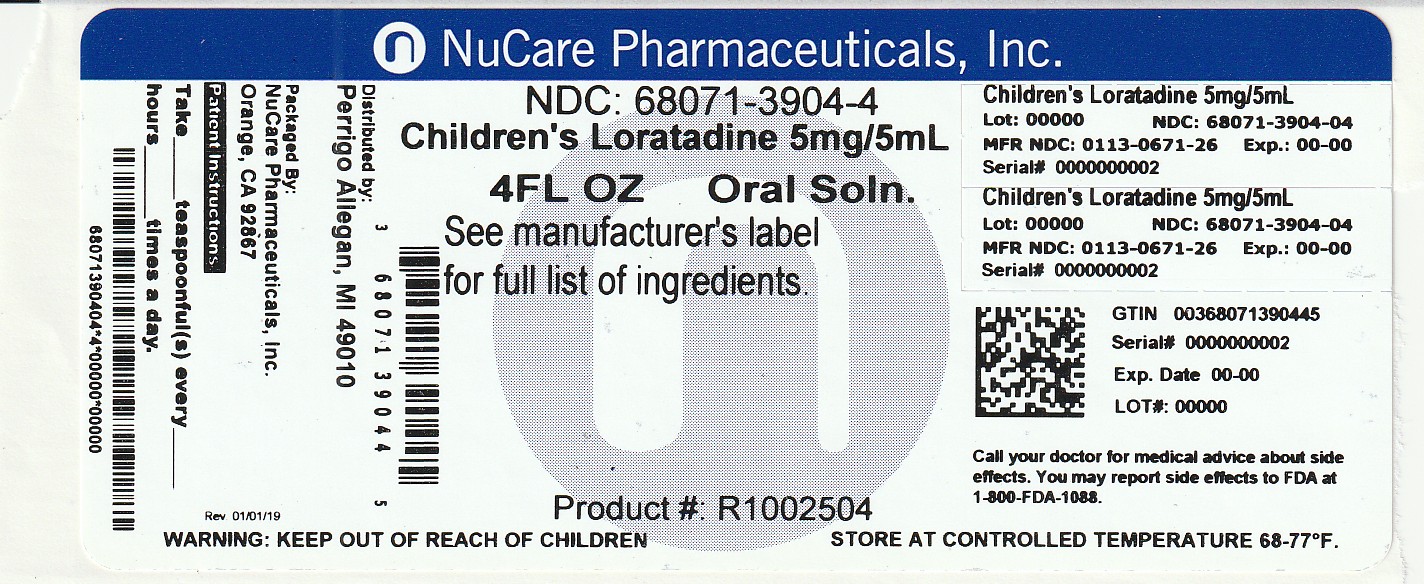 DRUG LABEL: Good Sense childrens allergy relief
NDC: 68071-3904 | Form: SOLUTION
Manufacturer: NuCare Pharmaceuticals,Inc.
Category: otc | Type: HUMAN OTC DRUG LABEL
Date: 20251010

ACTIVE INGREDIENTS: LORATADINE 5 mg/5 mL
INACTIVE INGREDIENTS: EDETATE DISODIUM; GLYCERIN; MALTITOL; SODIUM PHOSPHATE, MONOBASIC, UNSPECIFIED FORM; PHOSPHORIC ACID; PROPYLENE GLYCOL; WATER; SODIUM BENZOATE; SORBITOL; SUCRALOSE

Perrigo Children’s Allergy Relief Drug Facts

Active ingredient (in each 5 mL teaspoonful)

Loratadine 5 mg

Purpose

Antihistamine

Uses

temporarily relieves these symptoms due to hay fever or other upper respiratory allergies:

- runny nose
- itchy, watery eyes
- sneezing
- itching of the nose or throat

Do not use

if you have ever had an allergic reaction to this product or any of its ingredients

Ask a doctor before use if you have

liver or kidney disease. Your doctor should determine if you need a different dose.

When using this product

do not take more than directed. Taking more than directed may cause drowsiness.

Stop use and ask a doctor if

an allergic reaction to this product occurs. Seek medical help right away.

If pregnant or breast feeding,

ask a health professional before use.

Keep out of reach of children.

In case of overdose, get medical help or contact a Poison Control Center right away (1-800-222-1222).

Directions

- use only with enclosed dosing cup

adults and children 6 years and over | 2 teaspoonfuls (tsp) daily; do not take more than 2 teaspoonfuls (tsp) in 24 hours
children 2 to under 6 years of age | 1 teaspoonful (tsp) daily; do not take more than 1 teaspoonful (tsp) in 24 hours
children under 2 years of age | ask a doctor
consumers with liver or kidney disease | ask a doctor

Other information

- do not use if carton is opened, or if printed neckband is broken or missing
- store between 20° to 25°C (68° to 77°F)

Inactive ingredients

edetate disodium, glycerin, maltitol, monobasic sodium phosphate, natural and artificial grape flavor, phosphoric acid, propylene glycol, purified water, sodium benzoate, sorbitol, sucralose

Questions or comments?

1-800-719-9260